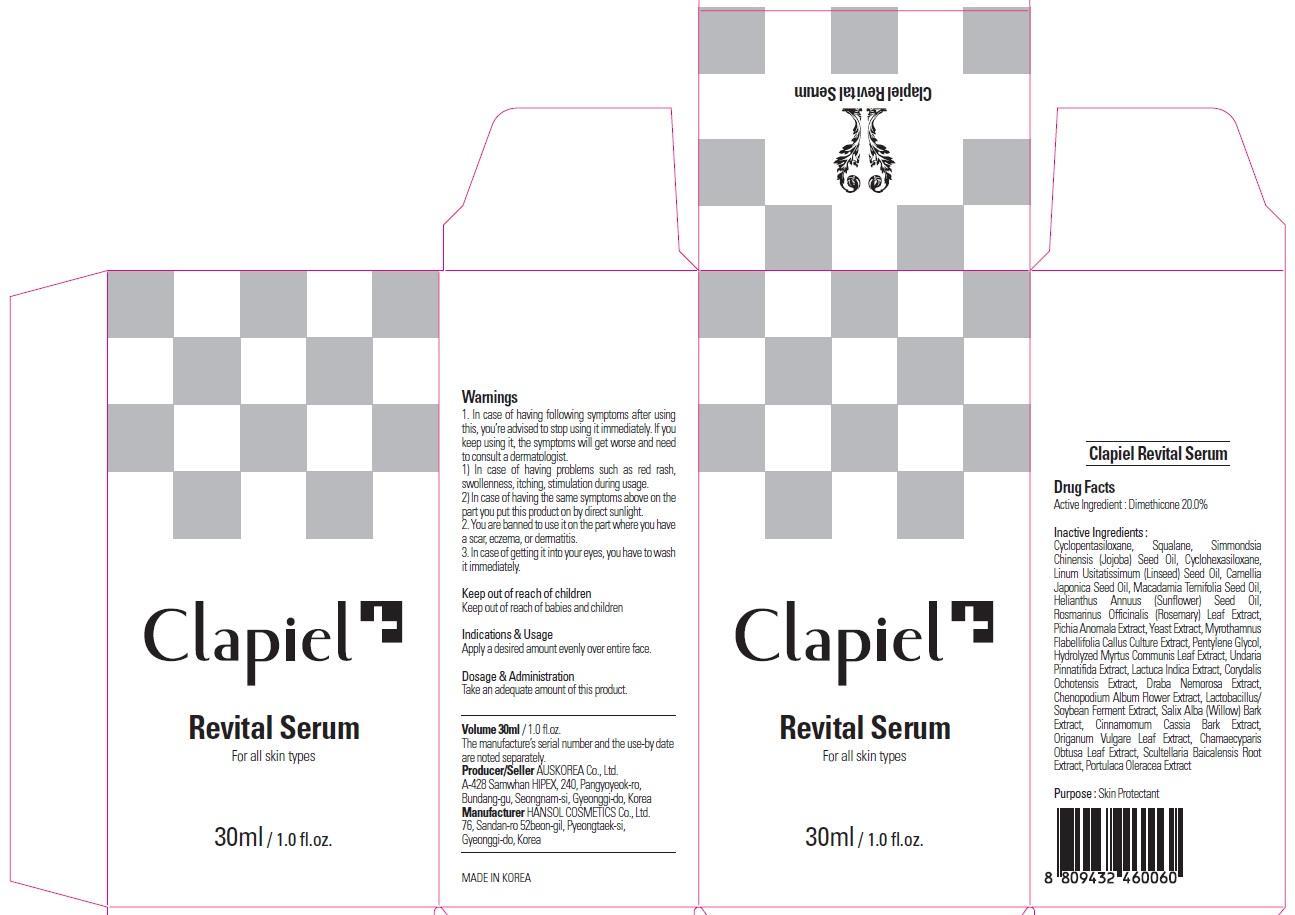 DRUG LABEL: Clapiel Revital Serum
NDC: 69977-040 | Form: CREAM
Manufacturer: AUS KOREA CO., LTD.
Category: otc | Type: HUMAN OTC DRUG LABEL
Date: 20150724

ACTIVE INGREDIENTS: Dimethicone 6.0 mg/30 mL
INACTIVE INGREDIENTS: Squalane; JOJOBA OIL

ACTIVE INGREDIENT

Active Ingredient: Dimethicone 20.0%

INACTIVE INGREDIENT

Inactive Ingredients: Cyclopentasiloxane, Squalane, Simmondsia Chinensis (Jojoba) Seed Oil, Cyclohexasiloxane, Linum Usitatissimum (Linseed) Seed Oil, Camellia Japonica Seed Oil, Macadamia Ternifolia Seed Oil, Helianthus Annuus (Sunflower) Seed Oil, Rosmarinus Officinalis (Rosemary) Leaf Extract, Pichia Anomala Extract, Yeast Extract, Myrothamnus Flabellifolia Callus Culture Extract, Pentylene Glycol, Hydrolyzed Myrtus Communis Leaf Extract, Undaria Pinnatifida Extract, Lactuca Indica Extract, Corydalis Ochotensis Extract, Draba Nemorosa Extract, Chenopodium Album Flower Extract, Lactobacillus/Soybean Ferment Extract, Salix Alba (Willow) Bark Extract, Cinnamomum Cassia Bark Extract, Origanum Vulgare Leaf Extract, Chamaecyparis Obtusa Leaf Extract, Scultellaria Baicalensis Root Extract, Portulaca Oleracea Extract

PURPOSE

Purpose: Skin Protectant

WARNINGS

Warnings: 1. In case of having following symptoms after using this, you’re advised to stop using it immediately. If you keep using it, the symptoms will get worse and need to consult a dermatologist. 1) In case of having problems such as red rash, swollenness, itching, stimulation during usage. 2) In case of having the same symptoms above on the part you put this product on by direct sunlight. 2. You are banned to use it on the part where you have a scar, eczema, or dermatitis. 3. In case of getting it into your eyes, you have to wash it immediately.

KEEP OUT OF REACH OF CHILDREN

Keep out of reach of babies and children

INDICATIONS & USAGE

Indications & Usage: Apply a desired amount evenly over entire face.

DOSAGE & ADMINISTRATION

Dosage & Administration: Take an adequate amount of this product.